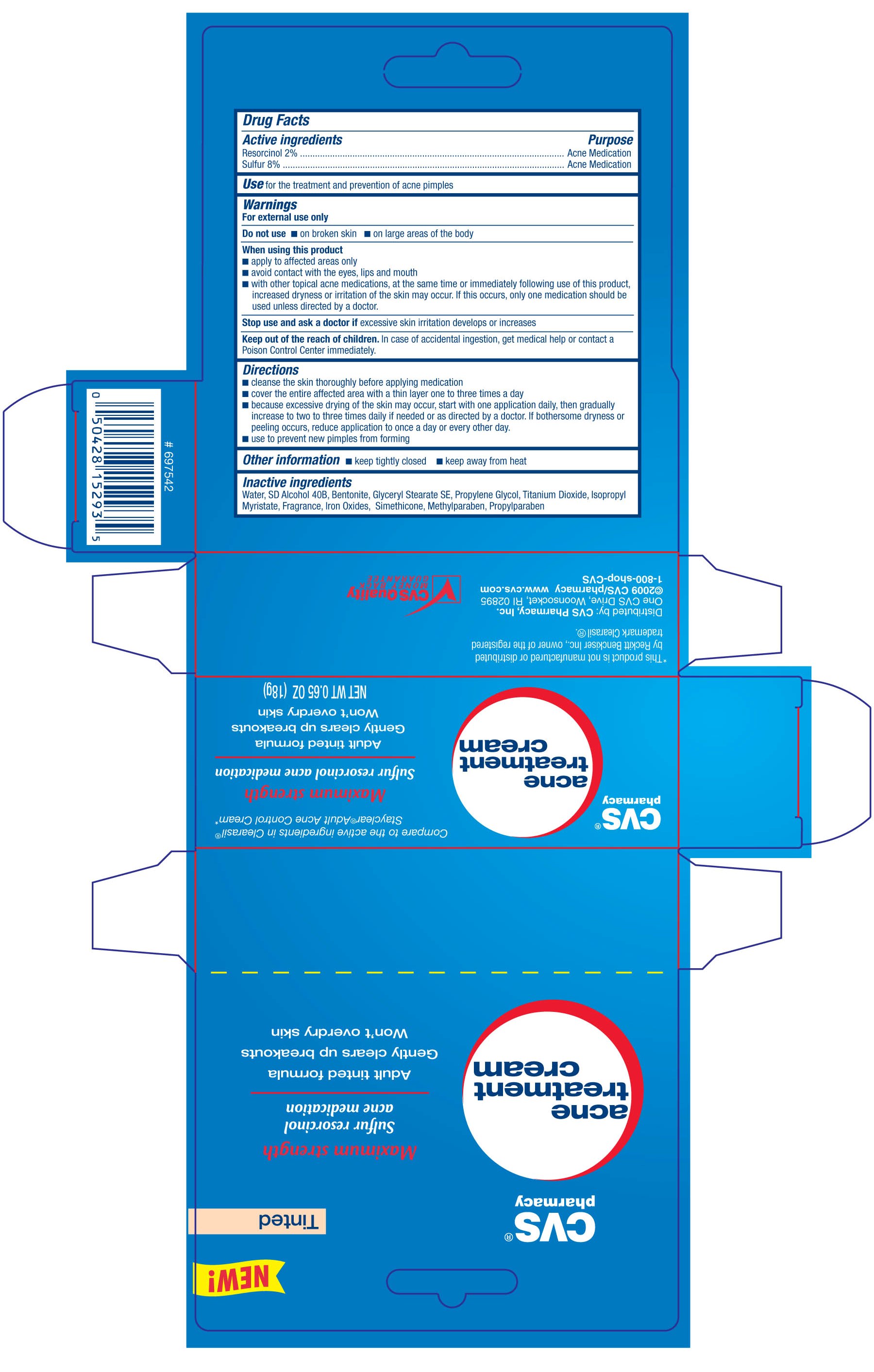 DRUG LABEL: CVS ACNE TREATMENT
NDC: 59779-813 | Form: CREAM
Manufacturer: CVS Pharmacy
Category: otc | Type: HUMAN OTC DRUG LABEL
Date: 20100710

ACTIVE INGREDIENTS: RESORCINOL 20 mg/1 g; SULFUR 80 mg/1 g
INACTIVE INGREDIENTS: WATER; BENTONITE; GLYCERYL MONOSTEARATE; TITANIUM DIOXIDE; ISOPROPYL MYRISTATE; DIMETHICONE; FERRIC OXIDE RED; TALC; ALCOHOL; METHYLPARABEN; PROPYLPARABEN

DRUG FACTS

Active ingredient Purpose
Resorcinol 2%............................................Acne medication
Sulfur 8%...................................................Acne Medication

PURPOSE

Uses for the treatment and prevention of acne pimples

Keep out of reach of children. In case of accidental ingestion, get medical help or contact a
Poison Control Center immediately.

INDICATIONS AND USAGE

Use for the treatment and prevention of acne pimples

Warnings
For external use only
Do not use - on broken skin - on large areas of the body
When using this product
- apply to affected areas only
- avoid contact with the eyes, lips and mouth
- with other topical acne medications, at the same time or immediately following use
of this product, increased dryness or irritation of the skin may occur.
If this occurs, only one medication should be used unless directed by a doctor.
Stop use and ask a doctor if excessive skin irritation develops or increases
Keep out of reach of children. In case of accidental ingestion, get medical help or contact a Poison
Control Center immediately.

Directions
- Cleanse the skin thoroughly before applying medication
- Cover the affected area with a thin layer one to three times a day
- because excessive drying of the skin may occur, start with one application daily,
then gradually increase to two to three times daily if needed or as directed by a doctor.
If bothersome dryness or peeling occurs, reduce application to once a day or every other day.
- use to prevent new pimples from forming
Other information
- keep tightly closed
- keep away from heat

Inactive Ingredients
Water, SD Alcohol 40B, Bentonite, Glyceryl Stearate SE, Propylene Glycol,
Titanium Dioxide, Isopropyl Myristate, Fragrance, Iron Oxides, Simethicone,
Methylparaben, Propylparaben